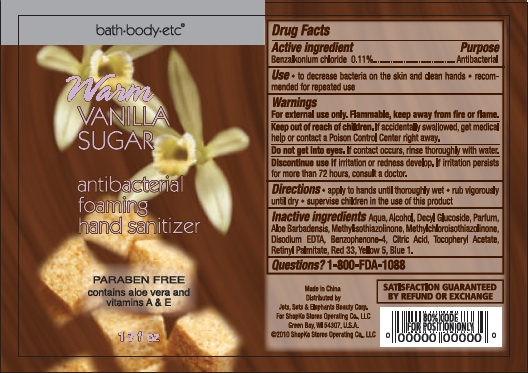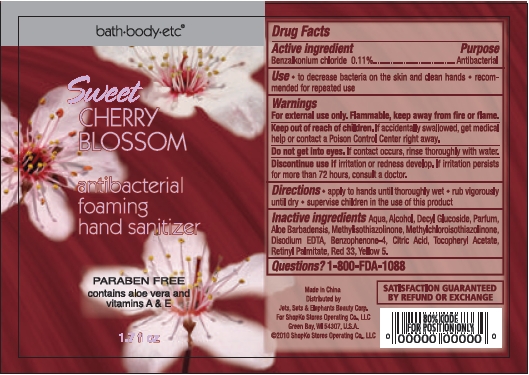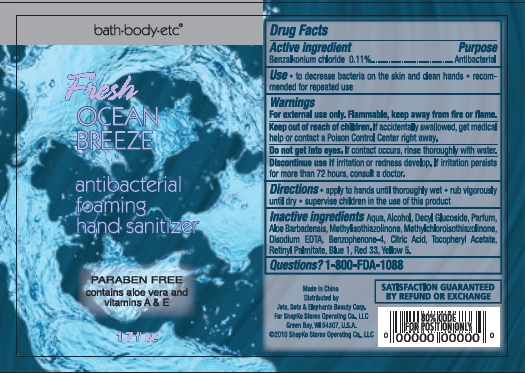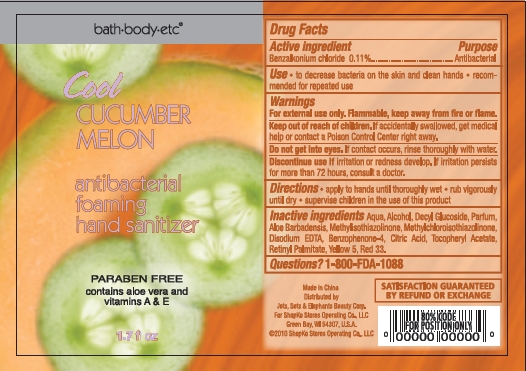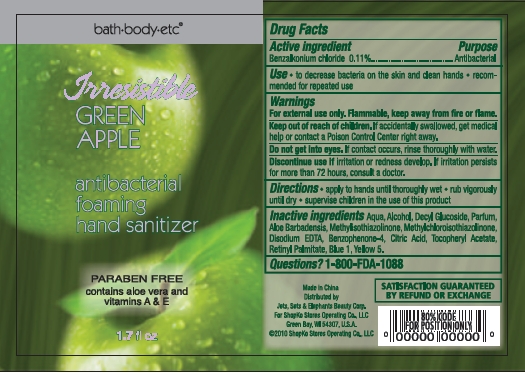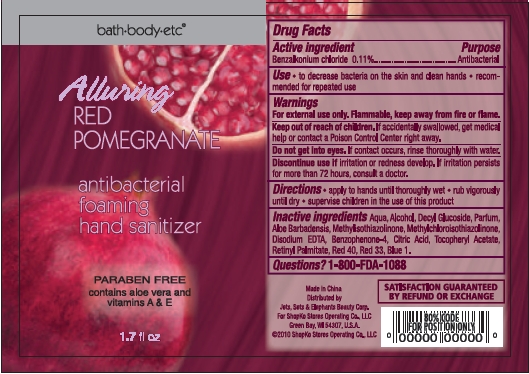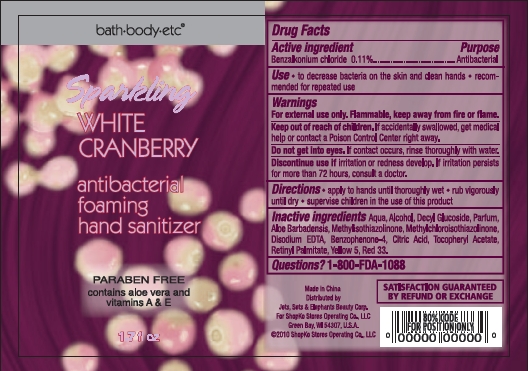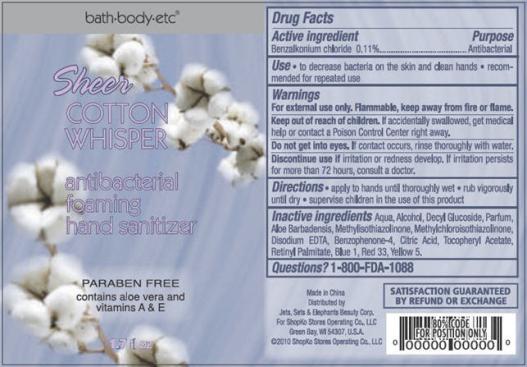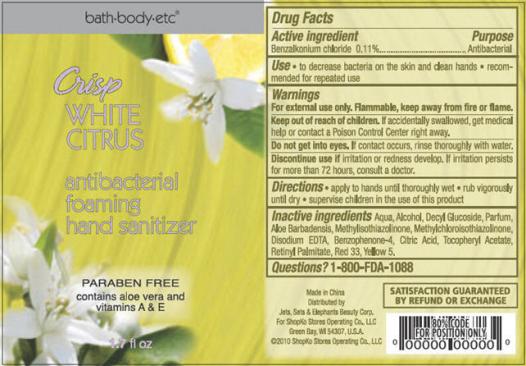 DRUG LABEL: Antibacterial Foaming Hand Sanitizer
NDC: 50988-190 | Form: SOLUTION
Manufacturer: Jets, Sets, & Elephants Beauty Corp.
Category: otc | Type: HUMAN OTC DRUG LABEL
Date: 20101124

ACTIVE INGREDIENTS: BENZALKONIUM CHLORIDE 0.055 mL/50.275 mL
INACTIVE INGREDIENTS: WATER; ALCOHOL; ALOE VERA LEAF; METHYLISOTHIAZOLINONE; METHYLCHLOROISOTHIAZOLINONE; EDETATE CALCIUM DISODIUM ANHYDROUS; SULISOBENZONE; CITRIC ACID MONOHYDRATE; .ALPHA.-TOCOPHEROL ACETATE, D-; VITAMIN A PALMITATE; D&C RED NO. 33; FD&C BLUE NO. 1; FD&C YELLOW NO. 5

bath+body+etc® antibacterial foaming hand sanitizer - Warm Vanilla Sugar, Sweet Cherry Blossom, Fresh Ocean Breeze, Cool Cucumber Melon, Irresistible Green Apple, Alluring Red Pomegranate, Sparkling White Cranberry, Crisp White Citrus, Sheer Cotton Whisper

Active ingredient

Benzalkonium chloride 0.11%

Purpose

Antibacterial

Uses

- to decrease bacteria on the skin and clean hands
- recommended for repeated use

Warnings

For external use only. Flammable, keep away from fire or flame.

Keep out of reach of children.

If accidentally swallowed, get medical help or contact a Poison Control Center right away.

Do not get into eyes. If contact occurs, rinse thoroughly with water.

Discontinue use if irritation or redness develop. If irritation persists for more than 72 hours, consult a doctor.

Directions

- apply to hands until thoroughly wet
- rub vigorously until dry
- supervise children in the use of this product

Inactive Ingredients

Warm Vanilla Sugar

Aqua, Alcohol, Decyl Glucoside, Parfum, Aloe Barbadensis, Methylisothiazolinone, Methylchloroisothiazolinone, Disodium EDTA, Benzophenone-4, Citric Acid, Tocopheryl Acetate, Retinyl Palmitate, Red 33, Blue 1, Yellow 5

Sweet Cherry Blossom

Aqua, Alcohol, Decyl Glucoside, Parfum, Aloe Barbadensis, Methylisothiazolinone, Methylchloroisothiazolinone, Disodium EDTA, Benzophenone-4, Citric Acid, Tocopheryl Acetate, Retinyl Palmitate, Red 33, Yellow 5

Fresh Ocean Breeze

Aqua, Alcohol, Decyl Glucoside, Parfum, Aloe Barbadensis, Methylisothiazolinone, Methylchloroisothiazolinone, Disodium EDTA, Benzophenone-4, Citric Acid, Tocopheryl Acetate, Retinyl Palmitate, Red 33, Blue 1, Yellow 5

Cool Cucumber Melon

Aqua, Alcohol, Decyl Glucoside, Parfum, Aloe Barbadensis, Methylisothiazolinone, Methylchloroisothiazolinone, Disodium EDTA, Benzophenone-4, Citric Acid, Tocopheryl Acetate, Retinyl Palmitate, Red 33, Yellow 5

Irresistible Green Apple

Aqua, Alcohol, Decyl Glucoside, Parfum, Aloe Barbadensis, Methylisothiazolinone, Methylchloroisothiazolinone, Disodium EDTA, Benzophenone-4, Citric Acid, Tocopheryl Acetate, Retinyl Palmitate, Blue 1, Yellow 5

Alluring Red Pomegranate

Aqua, Alcohol, Decyl Glucoside, Parfum, Aloe Barbadensis, Methylisothiazolinone, Methylchloroisothiazolinone, Disodium EDTA, Benzophenone-4, Citric Acid, Tocopheryl Acetate, Retinyl Palmitate, Red 40, Red 33, Blue 1

Sparkling White Cranberry

Aqua, Alcohol, Decyl Glucoside, Parfum, Aloe Barbadensis, Methylisothiazolinone, Methylchloroisothiazolinone, Disodium EDTA, Benzophenone-4, Citric Acid, Tocopheryl Acetate, Retinyl Palmitate, Red 33, Yellow 5

Crisp White Citrus

Aqua, Alcohol, Decyl Glucoside, Parfum, Aloe Barbadensis, Methylisothiazolinone, Methylchloroisothiazolinone, Disodium EDTA, Benzophenone-4, Citric Acid, Tocopheryl Acetate, Retinyl Palmitate, Red 33, Yellow 5

Sheer Cotton Whisper

Aqua, Alcohol, Decyl Glucoside, Parfum, Aloe Barbadensis, Methylisothiazolinone, Methylchloroisothiazolinone, Disodium EDTA, Benzophenone-4, Citric Acid, Tocopheryl Acetate, Retinyl Palmitate, Blue 1, Red 33, Yellow 5

Questions?

1-800-FDA-1088

SATISFACTION GUARANTEED BY REFUND OR EXCHANGE

Made in China

Distributed by Jets, Sets & Elephants Beauty Corp.

For Shopko Stores Operating Co., LLC

Green Bay, WI 54307, U.S.A.

©2010 Shopko Stores Operating Co., LLC

Package/Label Principal Display Panel - Bottle Label

bath+body+etc®

Warm

VANILLA SUGAR

antibacterial

foaming

hand sanitizer

PARABEN FREE

contains aloe vera and

vitamins A & E

1.7 fl oz

Warm Vanilla Sugar Bottle Label

Package/Label Principal Display Panel - Bottle Label

bath+body+etc®

Sweet

CHERRY BLOSSOM

antibacterial

foaming

hand sanitizer

PARABEN FREE

contains aloe vera and

vitamins A & E

1.7 fl oz

Sweet Cherry Blossom Bottle Label

Package/Label Principal Display Panel - Bottle Label

bath+body+etc®

Fresh

OCEAN BREEZE

antibacterial

foaming

hand sanitizer

PARABEN FREE

contains aloe vera and

vitamins A & E

1.7 fl oz

Fresh Ocean Breeze Bottle Label

Package/Label Principal Display Panel - Bottle Label

bath+body+etc®

Cool

CUCUMBER MELON

antibacterial

foaming

hand sanitizer

PARABEN FREE

contains aloe vera and

vitamins A & E

1.7 fl oz

Cool Cucumber Melon Bottle Label

Package/Label Principal Display Panel - Bottle Label

bath+body+etc®

Irresistible

GREEN APPLE

antibacterial

foaming

hand sanitizer

PARABEN FREE

contains aloe vera and

vitamins A & E

1.7 fl oz

Irresistible Green Apple Bottle Label

Package/Label Principal Display Panel - Bottle Label

bath+body+etc®

Alluring

RED POMEGRANATE

antibacterial

foaming

hand sanitizer

PARABEN FREE

contains aloe vera and

vitamins A & E

1.7 fl oz

Alluring Red Pomegranate Bottle Label

Package/Label Principal Display Panel - Bottle Label

bath+body+etc®

Sparkling

WHITE CRANBERRY

antibacterial

foaming

hand sanitizer

PARABEN FREE

contains aloe vera and

vitamins A & E

1.7 fl oz

Sparkling White Cranberry Bottle Label

Package/Label Principal Display Panel - Bottle Label

bath+body+etc®

Crisp

WHITE CITRUS

antibacterial

foaming

hand sanitizer

PARABEN FREE

contains aloe vera and

vitamins A & E

1.7 fl oz

Crisp White Citrus Bottle Label

Package/Label Principal Display Panel - Bottle Label

bath+body+etc®

Sheer

COTTON WHISPER

antibacterial

foaming

hand sanitizer

PARABEN FREE

contains aloe vera and

vitamins A & E

1.7 fl oz

Sheer Cotton Whisper Bottle Label